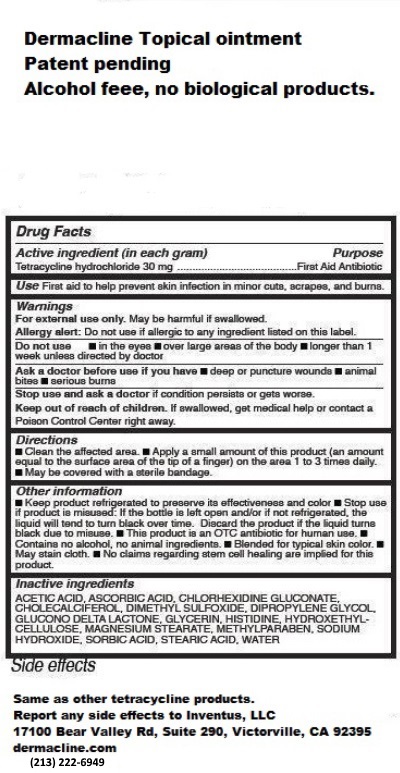 DRUG LABEL: Dermacline
NDC: 71250-002 | Form: OINTMENT
Manufacturer: Inventus, LLC
Category: otc | Type: HUMAN OTC DRUG LABEL
Date: 20161108

ACTIVE INGREDIENTS: TETRACYCLINE HYDROCHLORIDE 30 mg/1 mL
INACTIVE INGREDIENTS: ACETIC ACID; ASCORBIC ACID; CHLORHEXIDINE GLUCONATE; CHOLECALCIFEROL; DIMETHYL SULFOXIDE; DIPROPYLENE GLYCOL; GLYCERIN; HISTIDINE; MAGNESIUM STEARATE; METHYLPARABEN; SODIUM HYDROXIDE; SORBIC ACID; WATER

Dermacline

Active Ingredient (in each gram)

Tetracycline Hydrochloride 30mg

Purpose

First Aid antibiotic

Use

First aid to help prevent skin infection in minor cuts, scrapes, and burns.

Warnings

For esternam use only. May be harmful is swallowed.

Allergy alert: Do not use if allergic to any ingredient listed on this label.

Do not use

- In eyes
- over large areas of the body

- longer than 1 week unless directed by doctor

Ask a doctor before use if you have

- deep or puncture wounds
- animal bites
- serious trauma

Stop use and ask a doctor if condition persists or gets worse.

KEEP OUT OF REACH OF CHILDREN

Keep our of reach of children. If swallowed, get medical help or contact a Poison control Center right away.

Directions

- Clean the affected area
- Apply a small amount of this product (an amount equal to the surface area of the tip of a finger) on the area 1 to 3 times daily.
- May be covered with a sterile bandage.

Other Information

- Keep product refrigerated to preserve its effectiveness and color
- Stop use if product is misused
- This product is an OTC antibiotic for human use
- Contains no alcohol, no animal ingredients
- Blended for typical skin color
- May stain cloth
- No claims regarding stem cell healing are implied for this product.

Inactive Ingredient

Acetic Acid, Ascorbic Acid, chlorhexidine gluconate, cholecalciferol, dimethyl sulfoxide, dipropylene glycol, glucono delta lactone, GLYCERIN, histidine, hydroxethylc-cellulose, magnesium stearate, methylparaben, sodium hydroxide, sorbic acid, steric acid, water.